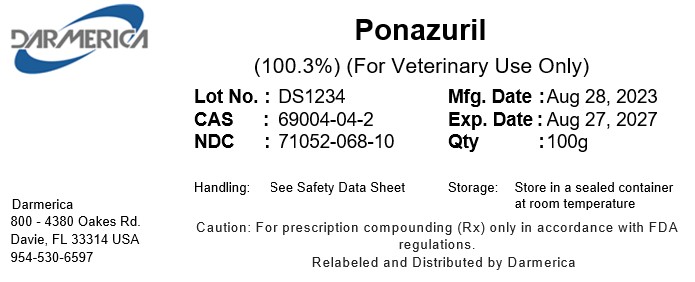 DRUG LABEL: Ponazuril
NDC: 71052-068 | Form: POWDER
Manufacturer: DARMERICA, LLC
Category: other | Type: BULK INGREDIENT - ANIMAL DRUG
Date: 20250220

ACTIVE INGREDIENTS: PONAZURIL 1 kg/1 kg

Ponazuril